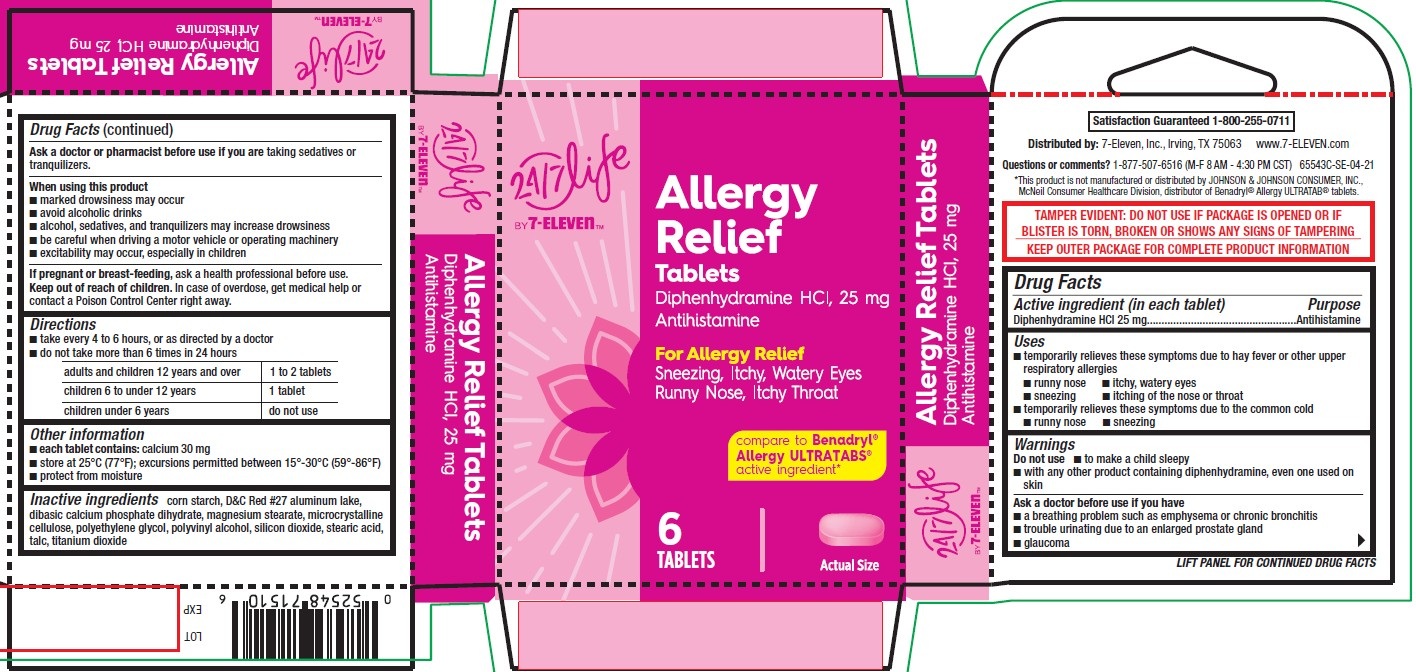 DRUG LABEL: Allergy Relief, 24-7 Life by 7-Eleven
NDC: 66715-8157 | Form: TABLET, FILM COATED
Manufacturer: Lil' Drug Store Products, Inc.
Category: otc | Type: HUMAN OTC DRUG LABEL
Date: 20251212

ACTIVE INGREDIENTS: DIPHENHYDRAMINE HYDROCHLORIDE 25 mg/1 1
INACTIVE INGREDIENTS: MICROCRYSTALLINE CELLULOSE; D&C RED NO. 27 ALUMINUM LAKE; DIBASIC CALCIUM PHOSPHATE DIHYDRATE; MAGNESIUM STEARATE; TALC; POLYVINYL ALCOHOL, UNSPECIFIED; STARCH, CORN; STEARIC ACID; SILICON DIOXIDE; POLYETHYLENE GLYCOL, UNSPECIFIED; TITANIUM DIOXIDE

Allergy Relief, 24/7 Life by 7-ElevenTM

Drug Facts

Active ingredient

Active ingredient (in each tablet)

Diphenhydramine HCl 25 mg

Purpose

Antihistamine

Uses

- temporarily relieves these symptoms due to hay fever or other upper respiratory allergies
- runny nose
- itchy, watery eyes
- sneezing
- itching of the nose or throat
- temporarily relieves these symptoms due to the common cold
- runny nose
- sneezing

Warnings

Do not use

- to make a child sleepy
- with any other product containing diphenhydramine, even one used on skin

Ask a doctor before use if you have

- a breathing problem such as emphysema or chronic bronchitis
- trouble urinating due to an enlarged prostate gland
- glaucoma

Ask a doctor or pharmacist before use if you are taking sedatives or tranquilizers.

When using this product

- marked drowsiness may occur
- avoid alcoholic drinks
- alcohol, sedatives, and tranquilizers may increase drowsiness
- be careful when driving a motor vehicle or operating machinery
- excitability may occur, especially in children

If pregnant or breast-feeding, ask a health professional before use.

Keep out of reach of children. In case of overdose, get medical help or contact a Poison Control Center right away.

Directions

- take every 4 to 6 hours, or as directed by a doctor
- do not take more than 6 times in 24 hours

adults and children 12 years and over | 1 to 2 tablets
children 6 to under 12 years | 1 tablet
children under 6 years | do not use

Other information

- each tablet contains: calcium 30 mg
- store at 25°C (77°F); excursions permitted between 15°-30°C (59°-86°F)
- protect from moisture

Inactive ingredients

corn starch, D&C Red #27 aluminum lake, dibasic calcium phosphate dihydrate, magnesium stearate, microcrystalline cellulose, polyethylene glycol, polyvinyl alcohol, silicon dioxide, stearic acid, talc, titanium dioxide

Allergy Relief, 24/7 Life by 7-ElevenTM

[ 24/7 Life by 7-ElevenTM logo]

Allergy

Relief

Tablets

Diphenhydramine HCl, 25 mg

Antihistamine

For Allergy Relief

Sneezing, Itchy, Watery Eyes

Runny Nose, Itchy Throat

compare to Benadryl®

Allergy ULTRATABS®

active ingredient*

6

TABLETS

[tablet image]

Actual Size